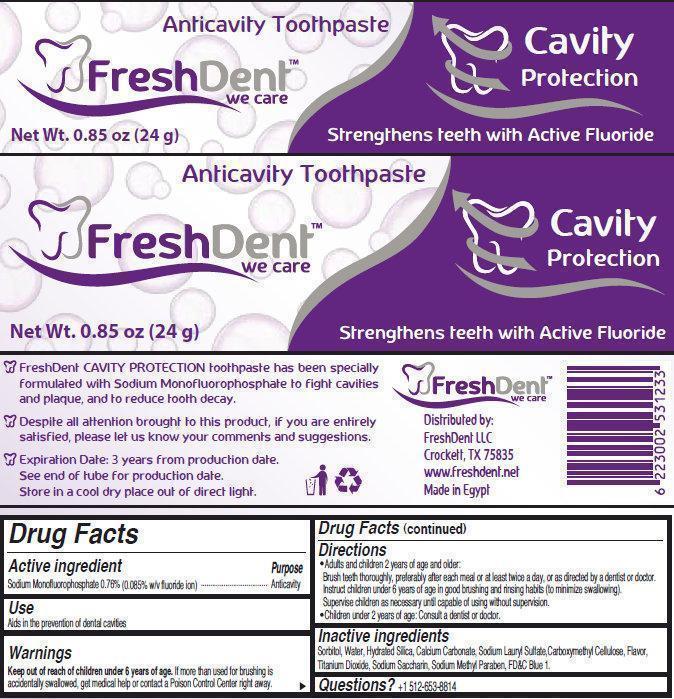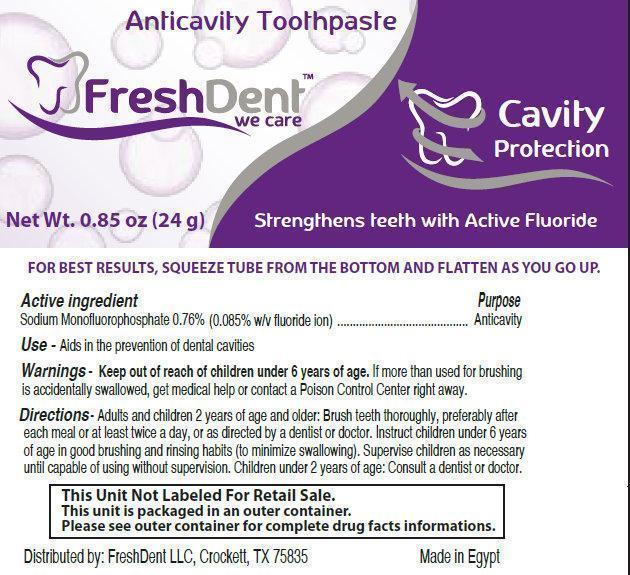 DRUG LABEL: FreshDent Cavity Protection Anticavity
NDC: 69338-002 | Form: PASTE, DENTIFRICE
Manufacturer: FreshDent LLC
Category: otc | Type: HUMAN OTC DRUG LABEL
Date: 20141106

ACTIVE INGREDIENTS: SODIUM MONOFLUOROPHOSPHATE 0.85 mg/1 g
INACTIVE INGREDIENTS: SORBITOL; GLYCERIN; WATER; SILICON DIOXIDE; CARBOXYMETHYLCELLULOSE; SODIUM LAURYL SULFATE; TITANIUM DIOXIDE; SACCHARIN SODIUM; METHYLPARABEN SODIUM; FD&C BLUE NO. 1

FreshDent Anticavity Toothpaste

Active Ingredients

Sodium Monofluorophosphate 0.76% (0.085% w/v fluoride ion)

Purpose

Anticavity

Use

Aids in the prevention of dental cavities

Keep out of reach of children under 6 years of age. If more than used for brushing is accidentally swallowed, get medical help or contact a Poison Control Center right away.

Directions

- Adults and children 2 years of age and older: Brush teeth thoroughly, preferably after each meal or at least twice a day, or as directed by a dentist or doctor. Instruct children under 6 years of age in good brushing and rinsing habits (to minimize swallowing). Supervise children as necessary until capable of using without supervision.

- Children under 2 years of age: Consult a dentist or doctor.

Inactive Ingredients

Sorbitol, Water, Hydrated Silica, Calcium Carbonate, Sodium Lauryl Sulfate,Carboxymethyl Cellulose, Flavor, Titanium Dioxide, Sodium Saccharin, Sodium Methyl Paraben, FD&C Blue 1.

Questions?

+1-512-653-8814

Package Label

Anticavity Toothpaste

FreshDent

we care

Cavity Protection

Strengthens teeth with Active Fluoride

Net Wt. 0.85 oz (24 g)

Distributed by: FreshDent LLC Crockett, TX 75835 www.freshdent.net Made in Egypt